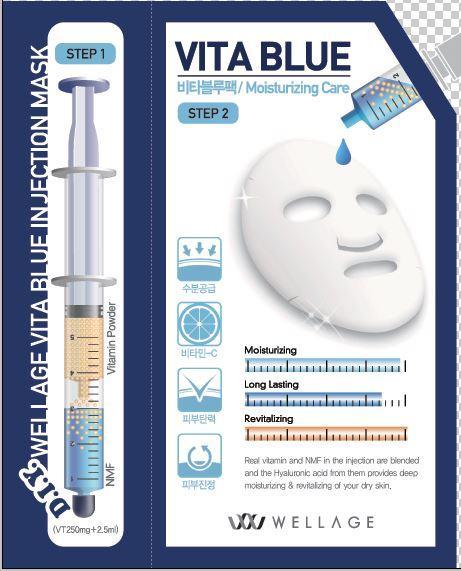 DRUG LABEL: WELLAGE Vita Blue Injec-tion Mask
NDC: 69346-1401 | Form: LIQUID
Manufacturer: HUGEL PHARMA CO.,LTD
Category: otc | Type: HUMAN OTC DRUG LABEL
Date: 20151028

ACTIVE INGREDIENTS: GLYCERIN 0.2 g/100 mL
INACTIVE INGREDIENTS: WATER; BUTYLENE GLYCOL; NIACINAMIDE

Drug Facts

ACTIVE INGREDIENT

glycerin

INACTIVE INGREDIENT

water, butylene glycol, niacinamide etc.

PURPOSE

anti-wrinkle

keep out of reach of the children

INDICATIONS AND USAGE

apply to the skin and leave for 10~20 minutes

WARNINGS

・Stop using the product when you have skin problems or the product disagrees with your skin
・Stop using the product immediately and consult a dermatologist if you have redness, swelling, itching or irritation on the skin while or after using the product.
・If the product gets into the eyes, don't rub but rinse with water.
・Don't place the product in any place where it will be subjected to extremely high or low temperatures or direct sunlight.

DOSAGE AND ADMINISTRATION

for external use only